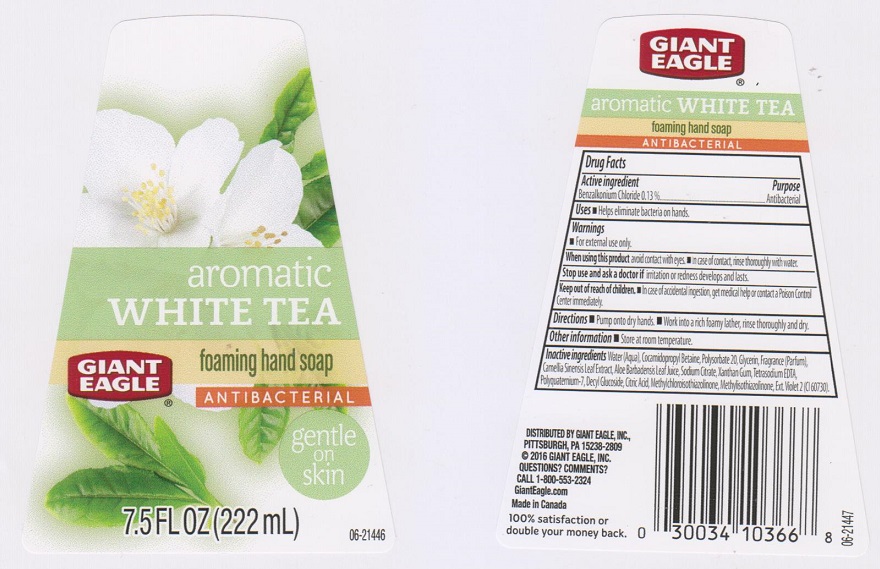 DRUG LABEL: Giant Eagle White Tea Foaming
NDC: 63148-273 | Form: LIQUID
Manufacturer: Apollo Health and Beauty Care
Category: otc | Type: HUMAN OTC DRUG LABEL
Date: 20161104

ACTIVE INGREDIENTS: BENZALKONIUM CHLORIDE 1.3 mg/1 mL
INACTIVE INGREDIENTS: WATER; COCAMIDOPROPYL BETAINE; POLYSORBATE 20; GLYCERIN; GREEN TEA LEAF; ALOE VERA LEAF; SODIUM CITRATE; XANTHAN GUM; EDETATE SODIUM; POLYQUATERNIUM-7 (70/30 ACRYLAMIDE/DADMAC; 1600000 MW); DECYL GLUCOSIDE; CITRIC ACID MONOHYDRATE; METHYLCHLOROISOTHIAZOLINONE; METHYLISOTHIAZOLINONE; EXT. D&C VIOLET NO. 2

Drug Facts

Active ingredient

Benzalkonium chloride 0.13%

Purpose

Antibacterial

Uses

Helps eliminate bacteria on hands.

Warnings

For external use only.

When using this product

avoid contact with eyes. In case of contact, rinse thoroughly with water.

Stop use and ask a doctor if

irritation or redness develops and lasts.

Keep out of reach of children.

In case of accidental ingestion, get medical help or contact a Poison Control Center immediately.

Directions

- Pump onto dry hands.
- Work into a rich foamy later, rinse thoroughly and dry.

Other information

Store at room temperature.

Inactive ingredients

Water (Aqua), Cocamidopropyl Betaine, Polysorbate 20, Glycerin, Fragrance (Parfum), Camellia Sinensis Leaf Extract, Aloe Barbadensis Leaf Juice, Sodium Citrate, Xanthan Gum, Tetrasodium EDTA, Polyquaternium-7, Decyl Glucoside, Citric Acid, Methylchloroisothiazolinone, Methylisothiazolinone, Ext. Violet 2 (CI 60730).